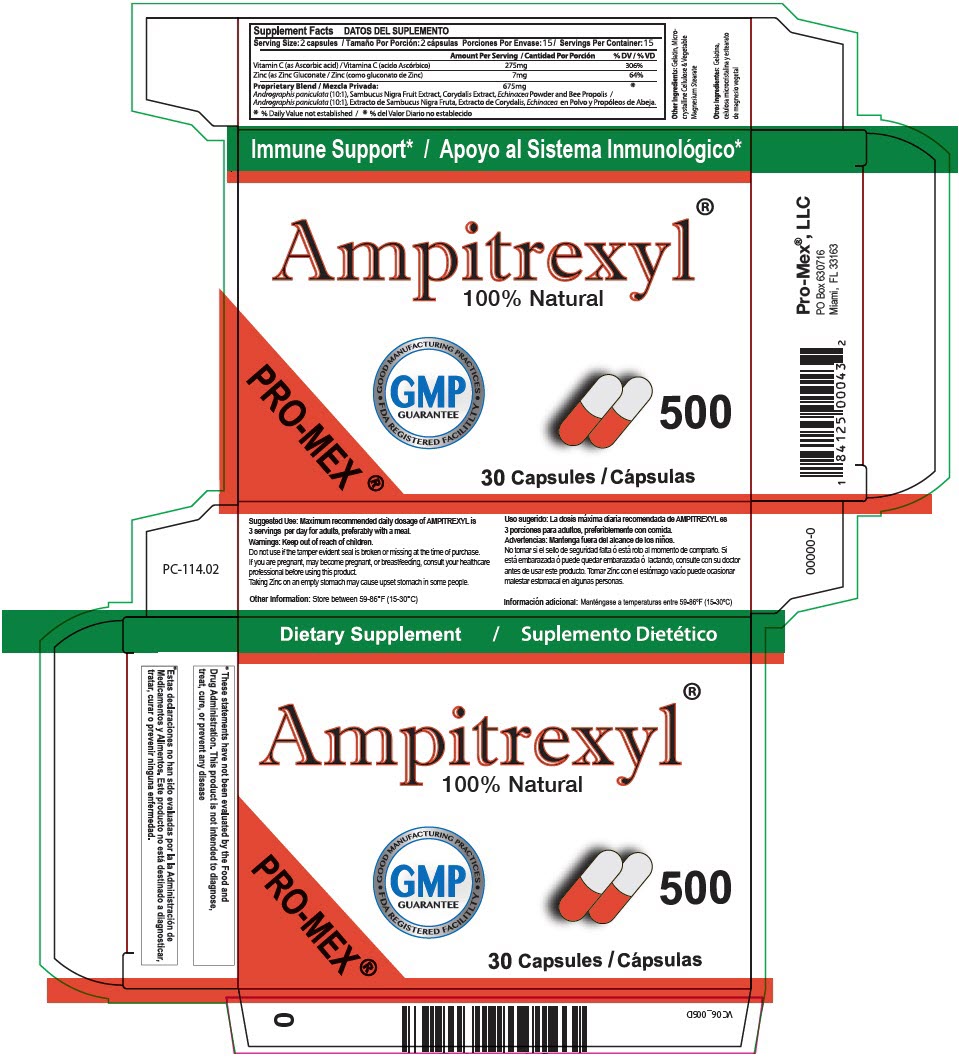 DRUG LABEL: AMPITREXYL
NDC: 58988-1141 | Form: CAPSULE
Manufacturer: ProMex LLC
Category: other | Type: DIETARY SUPPLEMENT
Date: 20250701

ACTIVE INGREDIENTS: ASCORBIC ACID 275 mg/1 1; ZINC GLUCONATE 7 mg/1 1
INACTIVE INGREDIENTS: ANDROGRAPHIS PANICULATA WHOLE; EUROPEAN ELDERBERRY; DICENTRA CANADENSIS ROOT; ECHINACEA, UNSPECIFIED; PROPOLIS WAX; GELATIN, UNSPECIFIED; MICROCRYSTALLINE CELLULOSE; MAGNESIUM STEARATE

Ampitrexyl®

STATEMENT OF IDENTITY

Supplement Facts
Serving Size: 2 capsules / Servings Per Container: 15
 | Amount Per Serving | % DV
Vitamin C (as Ascorbic acid) | 275mg | 306%
Zinc (as Zinc Gluconate | 7mg | 64%
Proprietary Blend | 675mg | [% Daily Value not established]
Andrographis paniculata (10:1), Sambucus Nigra Fruit Extract, Corydalis Extract, Echinacea Powder and Bee Propolis

Other Ingredients: Gelatin, Microcrystalline Cellulose & Vegetable Magnesium Stearate

Suggested Use

Maximum recommended daily dosage of AMPITREXYL is 3 servings per day for adults, preferably with a meal.

Warnings

Keep out of reach of children.

Do not use if the tamper evident seal is broken or missing at the time of purchase.

If you are pregnant, may become pregnant, or breastfeeding, consult your healthcare professional before using this product.

Taking Zinc on an empty stomach may cause upset stomach in some people.

Other Information

Store between 59-86°F (15-30°C)

HEALTH CLAIM

* These statements have not been evaluated by the Food and Drug Administration. This product is not intended to diagnose, treat, cure, or prevent any disease

Pro-Mex®, LLC
PO Box 630716
Miami, FL 33163

PRINCIPAL DISPLAY PANEL - 500 mg Capsule Blister Pack Carton

Dietary Supplement

Ampitrexyl®
100% Natural

PRO-MEX®

• GOOD MANUFACTURING PRACTICES •
GMP
GUARANTEE
FDA REGISTERED FACILITY

500

30 Capsules